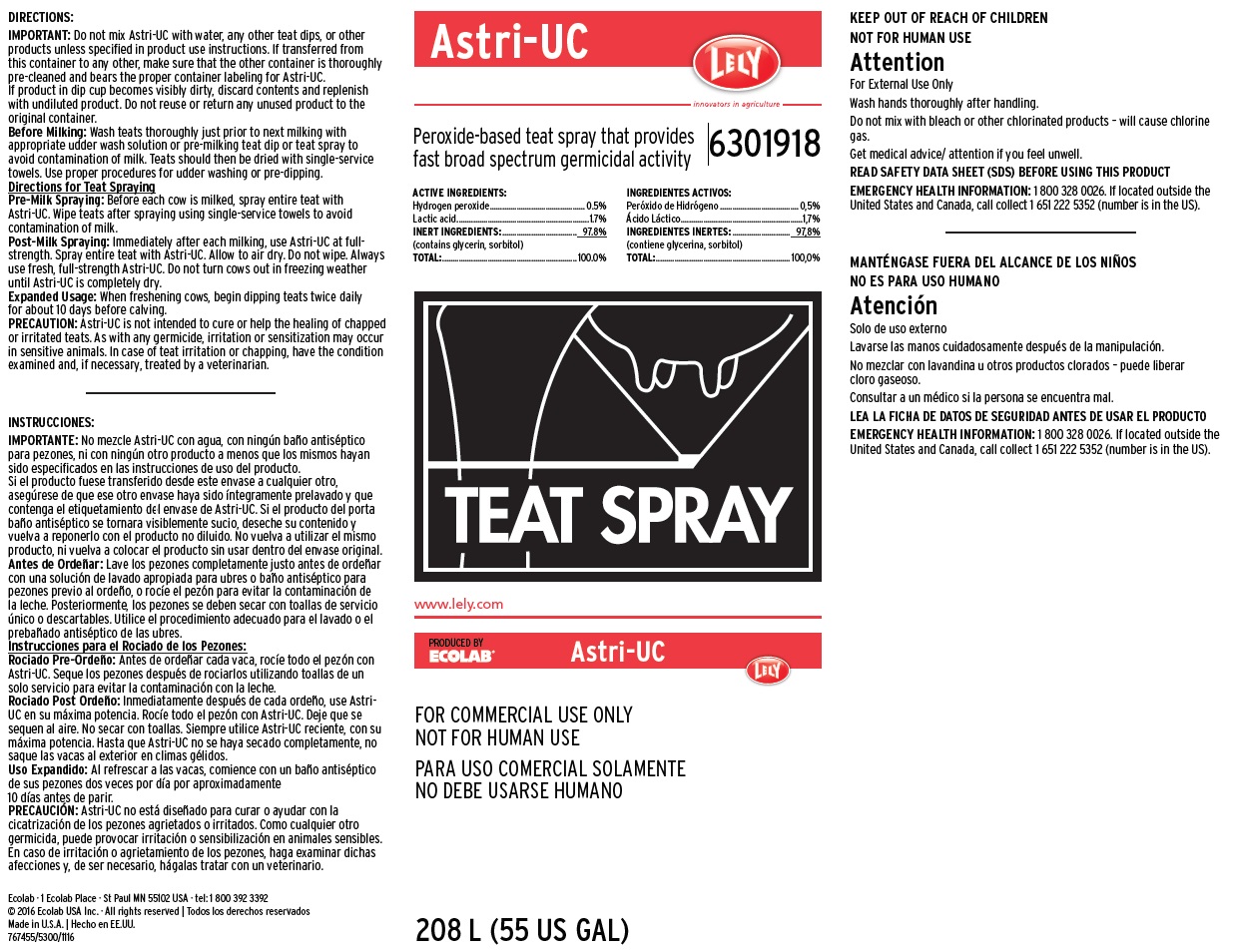 DRUG LABEL: Astri-UC
NDC: 47593-456 | Form: SOLUTION
Manufacturer: Ecolab Inc.
Category: animal | Type: OTC ANIMAL DRUG LABEL
Date: 20251030

ACTIVE INGREDIENTS: Hydrogen Peroxide 5 mg/1 mL; Lactic Acid 17 mg/1 mL
INACTIVE INGREDIENTS: Sorbitol; Glycerin

KEEP OUT OF REACH OF CHILDREN

NOT FOR HUMAN USE

Attention

For External Use Only

Wash hands thoroughly after handling.

Do not mix with bleach or other chlorinated products – will cause chlorine gas.

Get medical advice/ attention if you feel unwell.

DIRECTIONS:

IMPORTANT: Do not mix Astri-UC with water, any other teat dips, or other products unless specified in product use instructions. If transferred from this container to any other, make sure that the other container is thoroughly pre-cleaned and bears the proper container labeling for Astri-UC.

If product in dip cup becomes visibly dirty, discard contents and replenish with undiluted product. Do not reuse or return any unused product to the original container.

Before Milking: Wash teats thoroughly just prior to next milking with appropriate udder wash solution or pre-milking teat dip or teat spray to avoid contamination of milk. Teats should then be dried with single-service towels. Use proper procedures for udder washing or pre-dipping.

Directions for Teat Spraying

Pre-Milk Spraying: Before each cow is milked, spray entire teat with Astri-UC. Wipe teats after spraying using single-service towels to avoid contamination of milk.

Post-Milk Spraying: Immediately after each milking, use Astri-UC at full- strength. Spray entire teat with Astri-UC. Allow to air dry. Do not wipe. Always use fresh, full-strength Astri-UC. Do not turn cows out in freezing weather until Astri-UC is completely dry.

Expanded Usage: When freshening cows, begin dipping teats twice daily for about 10 days before calving.

PRECAUTION: Astri-UC is not intended to cure or help the healing of chapped or irritated teats. As with any germicide, irritation or sensitization may occur in sensitive animals. In case of teat irritation or chapping, have the condition examined and, if necessary, treated by a veterinarian.

OTHER SAFETY INFORMATION

READ SAFETY DATA SHEET (SDS) BEFORE USING THIS PRODUCT

EMERGENCY HEALTH INFORMATION: 1 800 328 0026. If located outside the United States and Canada, call collect 1 651 222 5352 (number is in the US).

PRINCIPAL DISPLAY PANEL/REPRESENTATIVE LABEL

ASTRI-UC
LELY
innovations in agriculture

Peroxide-based teat spray that provides

fast broad spectrum germicidal activity

6301918

ACTIVE INGREDIENTS:
Hydrogen Peroxide......................... 0.5%
Lactic Acid..................................... 1.7%

INERT INGREDIENTS:...................97.8%
(Contains glycerin, sorbitol)

TOTAL:..........................................100.0%

TEAT SPRAY

208 L (55 US GAL)

Ecolab · 1 Ecolab Place · St Paul MN 55102 USA · tel: 1 800 392 3392
© 2016 Ecolab USA Inc. · All rights reserved | Todos los derechos reservados
Made in U.S.A. | Hecho en EE.UU.
767455/5300/1116